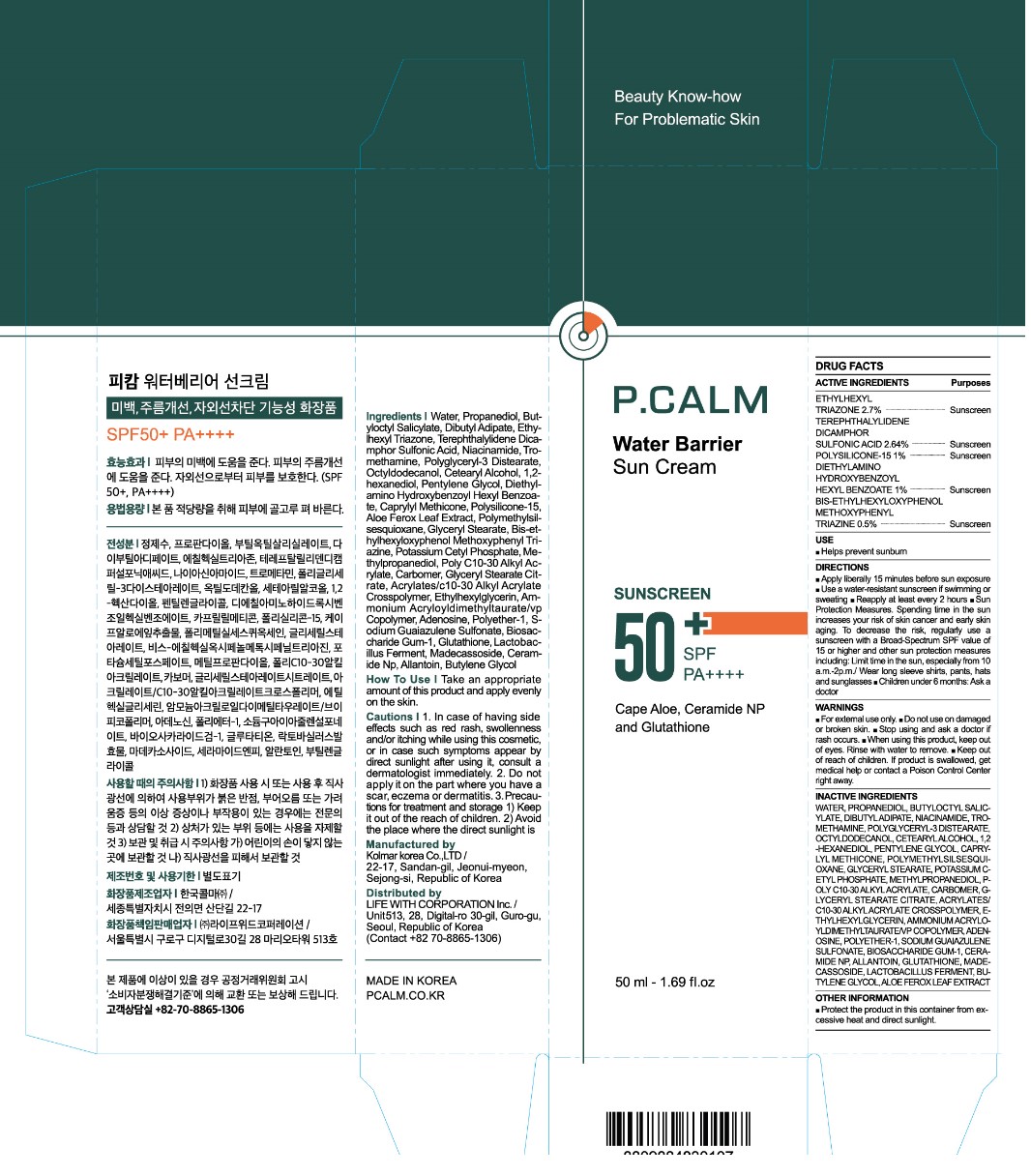 DRUG LABEL: P.CALM Water Barrier Suncream
NDC: 83735-001 | Form: CREAM
Manufacturer: LIFE WITH CORPORATION Inc.
Category: otc | Type: HUMAN OTC DRUG LABEL
Date: 20240702

ACTIVE INGREDIENTS: BEMOTRIZINOL 5 mg/1 mL; ETHYLHEXYL TRIAZONE 27 mg/1 mL; ECAMSULE 26.4 mg/1 mL; POLYSILICONE-15 10 mg/1 mL; DIETHYLAMINO HYDROXYBENZOYL HEXYL BENZOATE 10 mg/1 mL
INACTIVE INGREDIENTS: WATER; DIBUTYL ADIPATE; PROPANEDIOL; BUTYLOCTYL SALICYLATE; NIACINAMIDE; TROMETHAMINE; POLYGLYCERYL-3 DISTEARATE; OCTYLDODECANOL; 1,2-HEXANEDIOL; CETOSTEARYL ALCOHOL; PENTYLENE GLYCOL; CAPRYLYL TRISILOXANE; POLYMETHYLSILSESQUIOXANE (4.5 MICRONS); GLYCERYL MONOSTEARATE; POTASSIUM CETYL PHOSPHATE; METHYLPROPANEDIOL; BEHENYL ACRYLATE POLYMER; CARBOMER HOMOPOLYMER, UNSPECIFIED TYPE; GLYCERYL STEARATE CITRATE; ACRYLATES/C10-30 ALKYL ACRYLATE CROSSPOLYMER (60000 MPA.S); ETHYLHEXYLGLYCERIN; AMMONIUM ACRYLOYLDIMETHYLTAURATE/VP COPOLYMER; ADENOSINE; SODIUM GUALENATE; BIOSACCHARIDE GUM-1; CERAMIDE NP; ALLANTOIN; GLUTATHIONE; MADECASSOSIDE; BUTYLENE GLYCOL; ALOE FEROX LEAF

83735-001_P.CALM Water Barrier Sun Cream

ACTIVE INGREDIENT

ETHYLHEXYL TRIAZONE 2.7%
TEREPHTHALYLIDENE DICAMPHOR SULFONIC ACID 2.64%
POLYSILICONE-15 1%
DIETHYLAMINO HYDROXYBENZOYL HEXYL BENZOATE 1%
BIS-ETHYLHEXYLOXYPHENOL METHOXYPHENYL TRIAZINE 0.5%

PURPOSE

Sunscreen

INDICATIONS AND USAGE

Helps prevent sunburn

DOSAGE AND ADMINISTRATION

Apply liberally 15 minutes before sun exposure. Reapply at least every two hours

Sun protection measures. Spending time in the sun increases your risk of skin cancer and early skin aging. To decrease this risk, regularly use a sunscreen with a broad spectrum SPF of 15 of higher and other sun protection measures including: 1) Limited time in the sun, especially from 10 am to 2 pm. 2) Wear long-sleeve shirts, pants, hats, and sunglasses

Ask a doctor to use for children under 6 months

WARNINGS

For external use only

Do not use on damaged or broken skin

Stop using and ask a doctor if rash occurs

When using this product, keep out of eyes. Rinse with water to remove

Keep out of reach of children. If product is swallowed, get medical help or contact a Poison Control Center right away

INACTIVE INGREDIENT

WATER, PROPANEDIOL, BUTYLOCTYL SALICYLATE, DIBUTYL ADIPATE, NIACINAMIDE, TROMETHAMINE, POLYGLYCERYL-3 DISTEARATE, OCTYLDODECANOL, CETEARYL ALCOHOL, 1,2-HEXANEDIOL, PENTYLENE GLYCOL, CAPRYLYL METHICONE, POLYMETHYLSILSESQUIOXANE, GLYCERYL STEARATE, POTASSIUM CETYL PHOSPHATE, METHYLPROPANEDIOL, POLY C10-30 ALKYL ACRYLATE, CARBOMER, GLYCERYL STEARATE CITRATE, ACRYLATES/C10-30 ALKYL ACRYLATE CROSSPOLYMER, ETHYLHEXYLGLYCERIN, AMMONIUM ACRYLOYLDIMETHYLTAURATE/VP COPOLYMER, ADENOSINE, POLYETHER-1, SODIUM GUAIAZULENE SULFONATE, BIOSACCHARIDE GUM-1, CERAMIDE NP, ALLANTOIN, GLUTATHIONE, MADECASSOSIDE, LACTOBACILLUS FERMENT, BUTYLENE GLYCOL, ALOE FEROX LEAF EXTRACT